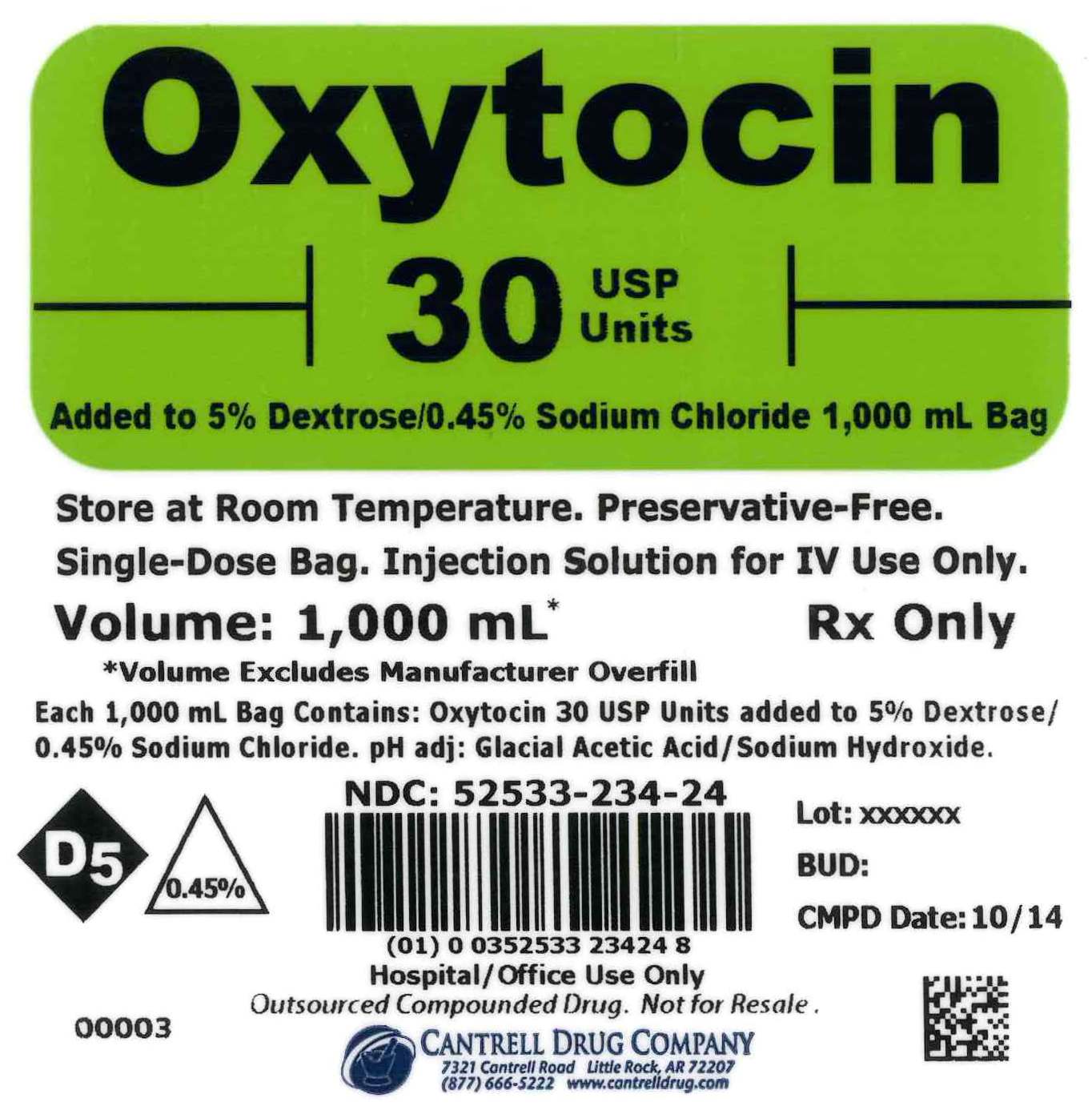 DRUG LABEL: Oxytocin
NDC: 52533-234 | Form: INJECTION, SOLUTION
Manufacturer: Cantrell Drug Company
Category: prescription | Type: HUMAN PRESCRIPTION DRUG LABEL
Date: 20160318

ACTIVE INGREDIENTS: OXYTOCIN 30 [USP'U]/1000 mL
INACTIVE INGREDIENTS: DEXTROSE MONOHYDRATE 50 g/1000 mL; SODIUM CHLORIDE 4.5 g/1000 mL; WATER

Oxytocin 30 USP Units Added to 5% Dextrose/0.45% Sodium Chloride 1,000 mL Bag